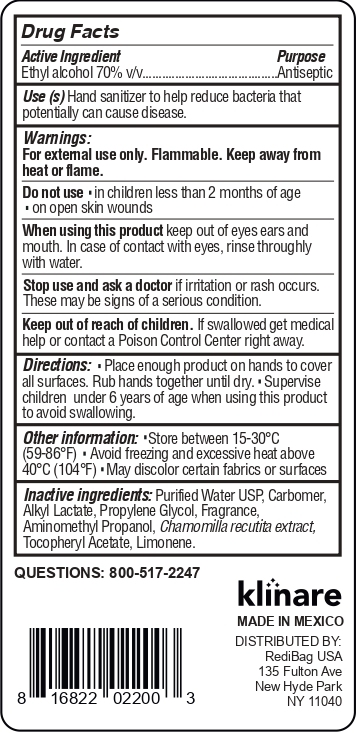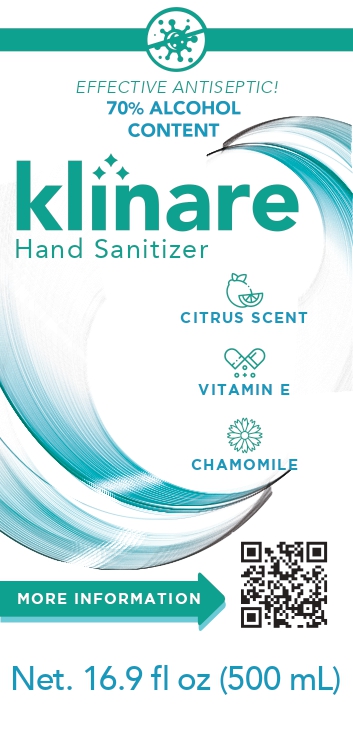 DRUG LABEL: Klinare Hand Sanitizer
NDC: 78342-003 | Form: GEL
Manufacturer: Química Blantex, S.A. de C.V.
Category: otc | Type: HUMAN OTC DRUG LABEL
Date: 20200731

ACTIVE INGREDIENTS: ALCOHOL 70 mL/100 mL
INACTIVE INGREDIENTS: AMINOMETHYLPROPANOL 0.1 mL/100 mL; CARBOMER HOMOPOLYMER, UNSPECIFIED TYPE 0.5 mL/100 mL; C12-15 ALKYL LACTATE 0.5 mL/100 mL; WATER 28.44 mL/100 mL; PROPYLENE GLYCOL 0.2 mL/100 mL; FRAGRANCE LEMON ORC2001060 0.2 mL/100 mL; MATRICARIA CHAMOMILLA WHOLE 0.05 mL/100 mL; ALPHA-TOCOPHEROL ACETATE 0.01 mL/100 mL; LIMONENE, (+)- 0.001 mL/100 mL

Klinare NDC 78342-003

Active Ingredient(s)

Alcohol 70% v/v. Purpose: Antiseptic

Purpose

Antiseptic, Hand Sanitizer

Use

Hand Sanitizer to help reduce bacteria that potentially can cause disease. For use when soap and water are not available.

Warnings

For external use only. Flammable. Keep away from heat or flame

Do not use

- in children less than 2 months of age
- on open skin wounds

When using this product keep out of eyes, ears, and mouth. In case of contact with eyes, rinse eyes thoroughly with water.
Stop use and ask a doctor if irritation or rash occurs. These may be signs of a serious condition.
Keep out of reach of children. If swallowed, get medical help or contact a Poison Control Center right away.

Stop use and ask a doctor if irritation or rash occurs. These may be signs of a serious condition.

Keep out of reach of children. If swallowed, get medical help or contact a Poison Control Center right away.

Directions

- Place enough product on hands to cover all surfaces. Rub hands together until dry.
- Supervise children under 6 years of age when using this product to avoid swallowing.

Other information

- Store between 15-30C (59-86F)
- Avoid freezing and excessive heat above 40C (104F)

Inactive ingredients

Purified Water USP, Carbomer, Alkyl Lactate, Propylene Glycol, Fragrance, Aminomethyl Propanol, Chamomilla Recutita Extract, Tocopheryl Acetate, Limonene

Package Label - Principal Display Panel

500 mL NDC: 78342-003-01